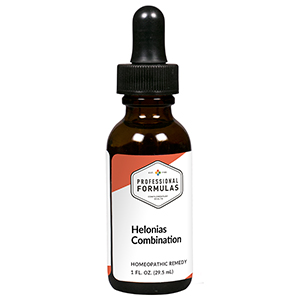 DRUG LABEL: Helonias Combination
NDC: 63083-9227 | Form: LIQUID
Manufacturer: Professional Complementary Health Formulas
Category: homeopathic | Type: HUMAN OTC DRUG LABEL
Date: 20190815

ACTIVE INGREDIENTS: VIBURNUM OPULUS BARK 2 [hp_X]/29.5 mL; APIS MELLIFERA 4 [hp_X]/29.5 mL; BLACK COHOSH 4 [hp_X]/29.5 mL; LILIUM LANCIFOLIUM WHOLE FLOWERING 4 [hp_X]/29.5 mL; LYCOPODIUM CLAVATUM SPORE 4 [hp_X]/29.5 mL; MELILOTUS OFFICINALIS TOP 4 [hp_X]/29.5 mL; PULSATILLA MONTANA WHOLE 4 [hp_X]/29.5 mL; VESPA CRABRO 4 [hp_X]/29.5 mL; CHAMAELIRIUM LUTEUM ROOT 6 [hp_X]/29.5 mL; AMMONIUM BROMIDE 8 [hp_X]/29.5 mL; GOLD MONOIODIDE 12 [hp_X]/29.5 mL; CHLAMYDIA TRACHOMATIS 12 [hp_X]/29.5 mL; LACHESIS MUTA VENOM 12 [hp_X]/29.5 mL; MERCURIC CHLORIDE 12 [hp_X]/29.5 mL; NAJA NAJA VENOM 12 [hp_X]/29.5 mL; PALLADIUM 12 [hp_X]/29.5 mL
INACTIVE INGREDIENTS: ALCOHOL; WATER

R227

ACTIVE INGREDIENTS

Viburnum opulus 2X
Apis mellifica 4X
Cimicifuga racemosa 4X
Lilium tigrinum 4X
Lycopodium clavatum 4X
Melilotus officinalis 4X
Pulsatilla 4X
Vespa crabro 4X
Helonias dioica 6X
Ammonium bromatum 8X
Aurum iodatum 12X
Chlamydia 12X
Lachesis mutus 12X
Mercurius corrosivus 12X
Naja tripudians 12X
Palladium metallicum 12X

QUESTIONS

Professional Formulas

PO Box 2034 Lake Oswego, OR 97035

INDICATIONS

For the temporary relief of mild to moderate pain, inflammation, nausea, or occasional headache associated with dysmenorrhea.*

PURPOSE

*Claims based on traditional homeopathic practice, not accepted medical evidence. Not FDA evaluated.

WARNINGS

In case of overdose, get medical help or contact a poison control center right away.

Keep out of the reach of children.

PREGNANCY OR BREAST FEEDING

If pregnant or breastfeeding, ask a healthcare professional before use.

DIRECTIONS

Place drops under tongue 30 minutes before/after meals. Adults and children 12 years and over: Take 10 drops up to 3 times per day. Consult a physician for use in children under 12 years of age.

OTHER INFORMATION

Tamper resistant. If seal is broken, do not use. After opening, close container tightly and store at room temperature away from heat.

INACTIVE INGREDIENTS

40% ethanol, purified water.

LABEL

Est 1985

Professional Formulas

Complementary Health

Helonias Combination

Homeopathic Remedy

1 FL. OZ. (29.5 mL)